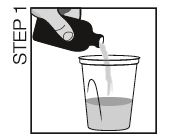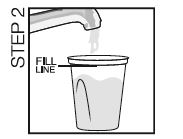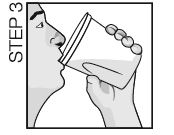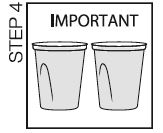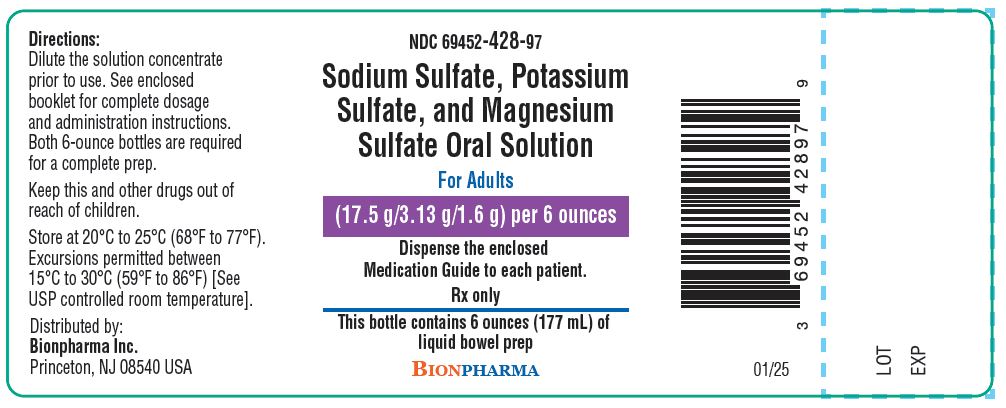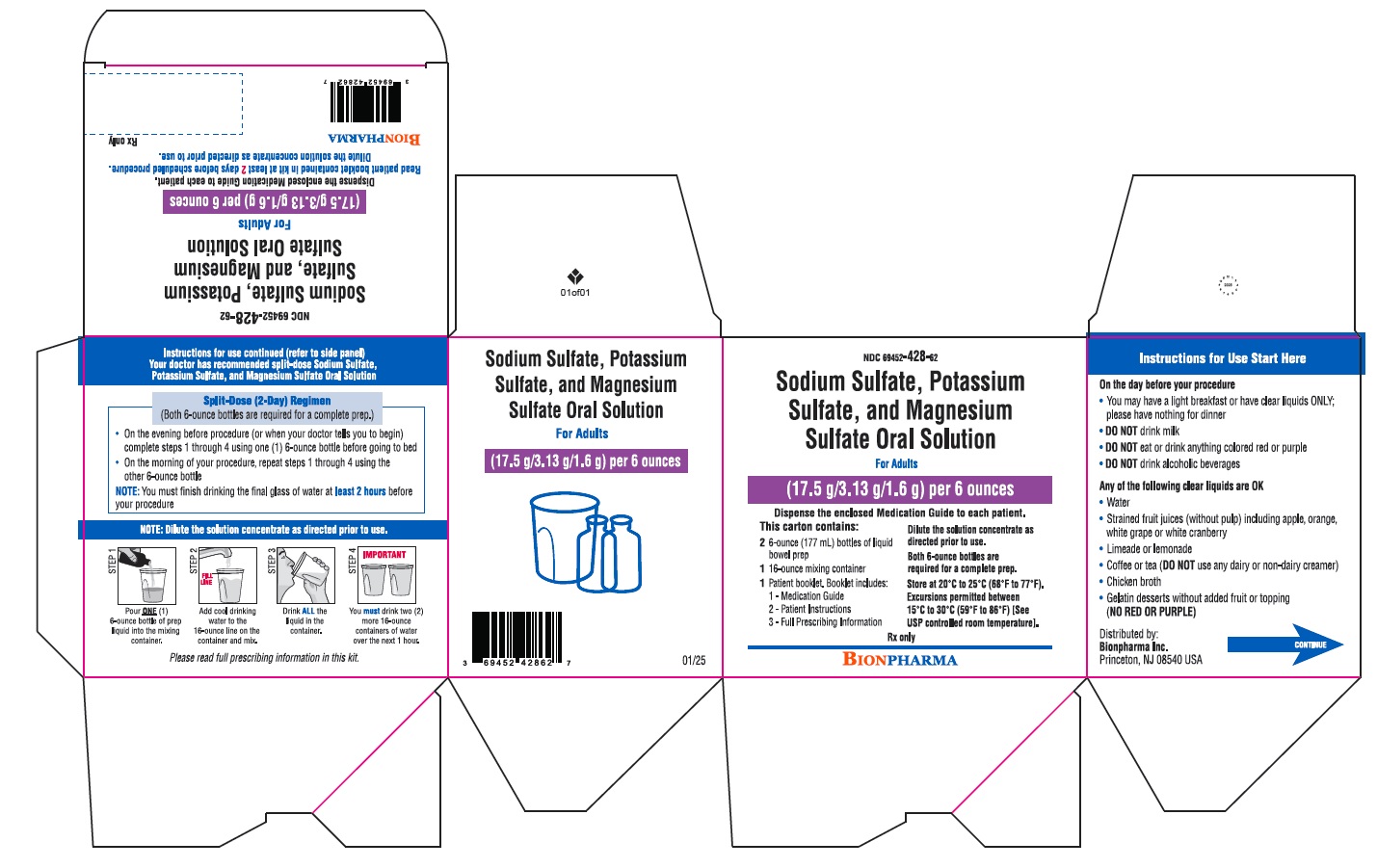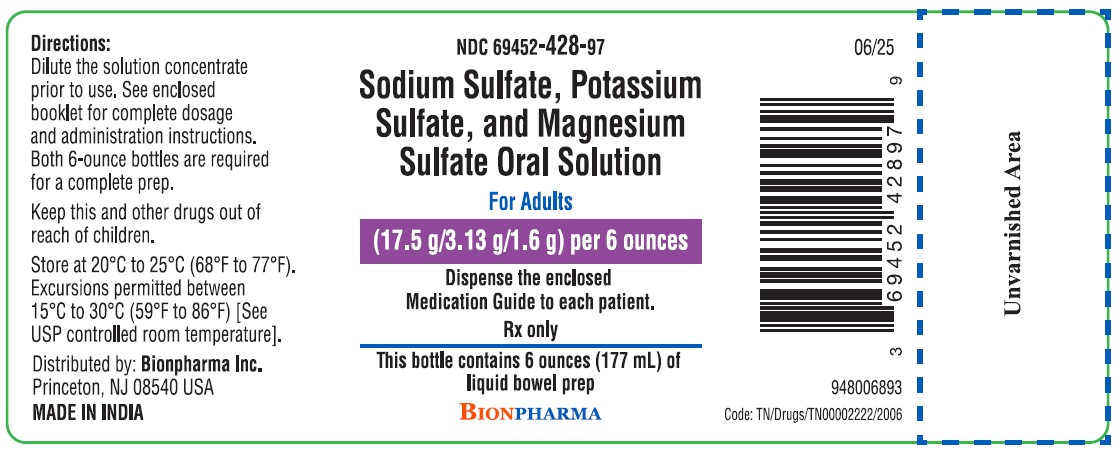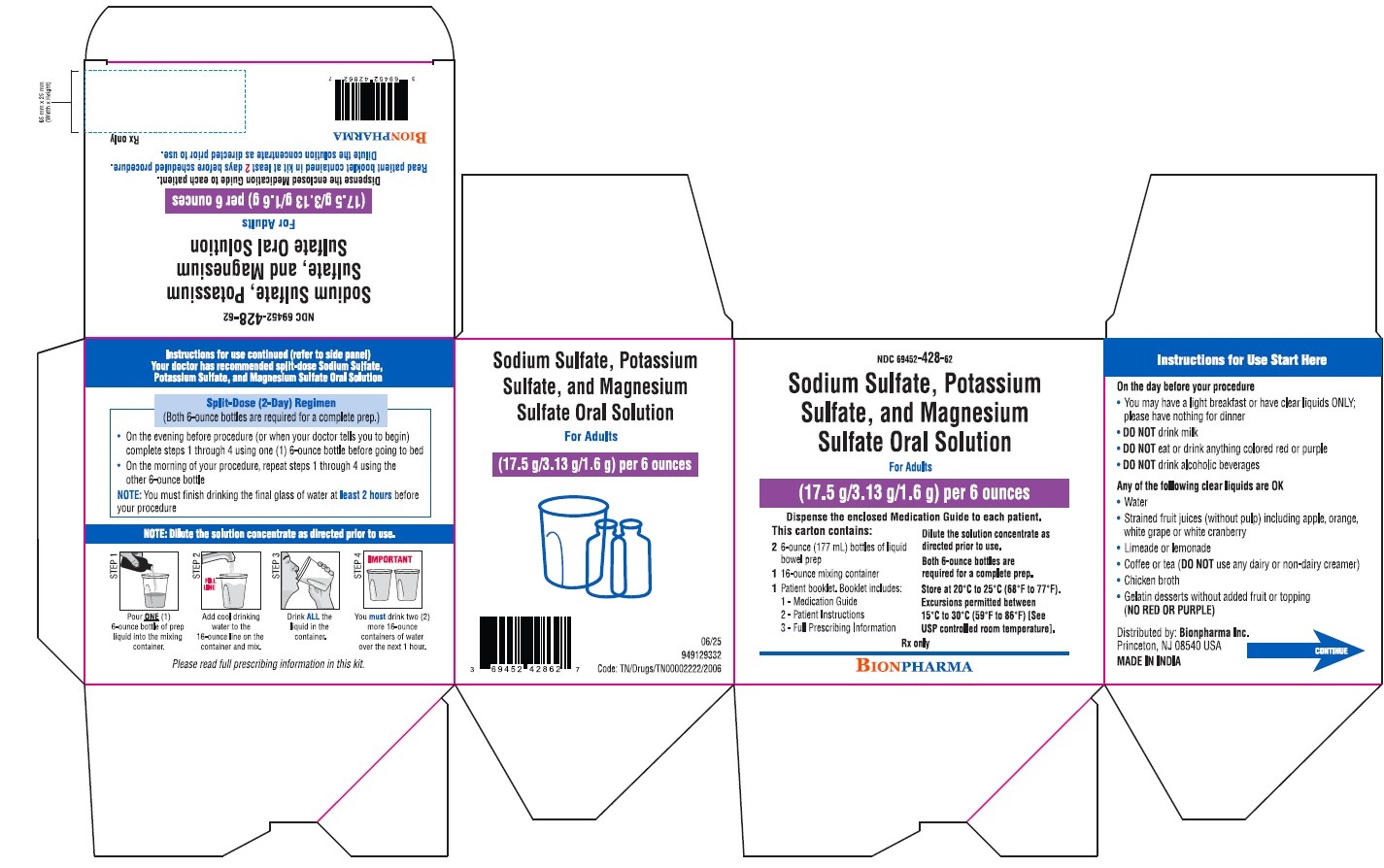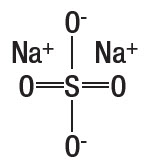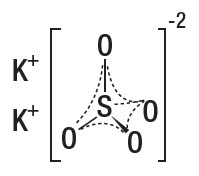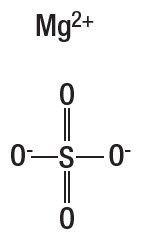 DRUG LABEL: sodium sulfate, potassium sulfate, and magnesium sulfate
NDC: 69452-428 | Form: SOLUTION
Manufacturer: Bionpharma Inc.,
Category: prescription | Type: HUMAN PRESCRIPTION DRUG LABEL
Date: 20260212

ACTIVE INGREDIENTS: SODIUM SULFATE 17.5 g/177 mL; POTASSIUM SULFATE 3.13 g/177 mL; MAGNESIUM SULFATE ANHYDROUS 1.6 g/177 mL
INACTIVE INGREDIENTS: SODIUM BENZOATE; SUCRALOSE; MALIC ACID; ANHYDROUS CITRIC ACID; WATER; BLUEBERRY

HIGHLIGHTS OF PRESCRIBING INFORMATION

These highlights do not include all the information needed to use SODIUM SULFATE, POTASSIUM SULFATE, AND MAGNESIUM SULFATE ORAL SOLUTION safely and effectively. See full prescribing information for SODIUM SULFATE, POTASSIUM SULFATE, AND MAGNESIUM SULFATE ORAL SOLUTION.
SODIUM SULFATE, POTASSIUM SULFATE, AND MAGNESIUM SULFATE oral solution
Initial U.S. Approval: 2010

1 INDICATIONS AND USAGE

Sodium sulfate, potassium sulfate, and magnesium sulfate oral solution is an osmotic laxative indicated for cleansing of the colon in preparation for colonoscopy in adult patients. (1)

2 DOSAGE AND ADMINISTRATION

Preparation and Administration (2.2)

- Must dilute in water prior to ingestion.
- Administration of two bottles of sodium sulfate, potassium sulfate, and magnesium sulfate oral solution is required for a complete preparation for colonoscopy. One bottle is equivalent to one dose.
- Must consume additional water after each dose.
- Stop consumption of all fluids at least 2 hours before the colonoscopy.

Recommended Dosage and Administration

- Split-Dose (two-day) regimen consists of two doses of sodium sulfate, potassium sulfate, and magnesium sulfate oral solution: first dose during the evening prior to colonoscopy and second dose the next day, during the morning of colonoscopy. (2.1, 2.3)
- Recommended sodium sulfate, potassium sulfate, and magnesium sulfate oral solution dosage is:
  - Adults:Two 6-ounce doses. (2.3)
- For complete information on preparation before colonoscopy and administration of the dosage regimen, see full prescribing Information. (2.1, 2.2, 2.3)

3 DOSAGE FORMS AND STRENGTHS

- Sodium sulfate, potassium sulfate, and magnesium sulfate oral solution (for adults): Two bottles each containing 6 ounces of an oral solution of 17.5 grams sodium sulfate, 3.13 grams potassium sulfate, and 1.6 grams magnesium sulfate. (3)

4 CONTRAINDICATIONS

- Gastrointestinal obstruction or ileus (4, 5.6)
- Bowel perforation (4, 5.6)
- Toxic colitis or toxic megacolon (4)
- Gastric retention (4)
- Hypersensitivity to any ingredient (4)

5 WARNINGS AND PRECAUTIONS

- Risk of fluid and electrolyte abnormalities: Encourage adequate hydration, assess concurrent medications, and consider laboratory assessments prior to and after each use. (5.1, 7.1)
- Cardiac arrhythmias: Consider pre-dose and post-colonoscopy ECGs in patients at increased risk. (5.2)
- Seizures: Use caution in patients with a history of seizures and patients at increased risk of seizures, including medications that lower the seizure threshold. (5.3, 7.1)
- Patients with renal impairment or taking concomitant medications that affect renal function: Use caution, ensure adequate hydration and consider laboratory testing. (5.4, 7.1)
- Suspected GI obstruction or perforation: Rule out the diagnosis before administration. (4, 5.6)
- Patients at risk for aspiration: Observe during administration. (5.7)

6 ADVERSE REACTIONS

Most common adverse reactions are:

- Adults (> 2%): overall discomfort, abdominal distention, abdominal pain, nausea, and vomiting. (6.1)

To report SUSPECTED ADVERSE REACTIONS, contact Bionpharma Inc. at 1-888-235-BION or 1-888-235-2466 or FDA at 1-800-FDA-1088 or www.fda.gov/medwatch.

7 DRUG INTERACTIONS

Drugs that increase risk of fluid and electrolyte imbalance. (7.1)

Pediatric use information is approved for Braintree Laboratories, Inc.'s SUPREP BOWEL PREP KIT (sodium sulfate, potassium sulfate, and magnesium sulfate) oral solution. However, due to Braintree Laboratories, Inc.'s marketing exclusivity rights, this drug product is not labeled with that pediatric information.

FULL PRESCRIBING INFORMATION

1 INDICATIONS AND USAGE

Sodium sulfate, potassium sulfate, and magnesium sulfate oral solution is indicated for cleansing of the colon as a preparation for colonoscopy in adult patients.

Pediatric use information is approved for Braintree Laboratories, Inc.'s SUPREP BOWEL PREP KIT (sodium sulfate, potassium sulfate, and magnesium sulfate) oral solution. However, due to Braintree Laboratories, Inc.'s marketing exclusivity rights, this drug product is not labeled with that pediatric information.

2 DOSAGE AND ADMINISTRATION

2.1 Dosage and Administration Overview

Administration of two bottles of sodium sulfate, potassium sulfate, and magnesium sulfate oral solution and additional water is required for a complete preparation for colonoscopy. One bottle of sodium sulfate, potassium sulfate, and magnesium sulfate oral solution is equivalent to one dose. Sodium sulfate, potassium sulfate, and magnesium sulfate oral solution is supplied in one dosage strength [see Dosage Forms and Strengths (3)] . The recommended dosage is:

- Adults:Two 6-ounce doses [see Dosage and Administration (2.3)] .

Pediatric use information is approved for Braintree Laboratories, Inc.'s SUPREP BOWEL PREP KIT (sodium sulfate, potassium sulfate, and magnesium sulfate) oral solution. However, due to Braintree Laboratories, Inc.'s marketing exclusivity rights, this drug product is not labeled with that pediatric information.

2.2 Important Preparation and Administration Instructions

- Correct fluid and electrolyte abnormalities before treatment with sodium sulfate, potassium sulfate, and magnesium sulfate oral solution [see Warnings and Precautions (5.1)].
- Must dilute sodium sulfate, potassium sulfate, and magnesium sulfate oral solution in water before ingestion.
- Must consume additional water after each dose of sodium sulfate, potassium sulfate, and magnesium sulfate oral solution.
- On the day before colonoscopy, consume only a light breakfast or clear liquids (e.g., water, strained fruit juice without pulp, lemonade, plain coffee or tea, chicken broth gelatin dessert without fruit). On the day of the colonoscopy only consume clear liquids up to two hours prior to colonoscopy.
- Do not eat solid food or drink milk or eat or drink anything colored red or purple.
- Do not drink alcohol.
- Do not take other laxatives while taking sodium sulfate, potassium sulfate, and magnesium sulfate oral solution.
- Do not take oral medications within one hour of starting each dose of sodium sulfate, potassium sulfate, and magnesium sulfate oral solution.
- If taking tetracycline or fluoroquinolone antibiotics, iron, digoxin, chlorpromazine, or penicillamine, take these medications at least 2 hours before and not less than 6 hours after administration of sodium sulfate, potassium sulfate, and magnesium sulfate oral solution [see Drug Interactions (7.2)] .
- Stop consumption of all fluids at least 2 hours prior to the colonoscopy.

2.3 Recommended Dosage and Administration for Adults

The recommended Split-Dose (two-day) regimen for adultsconsists of two 6-ounce doses of sodium sulfate, potassium sulfate, and magnesium sulfate oral solution: the first dose during the evening prior to colonoscopy and the second dose the next day, during the morning of the colonoscopy.

Each dose consists of one bottle of sodium sulfate, potassium sulfate, and magnesium sulfate oral solution with additional water. The total volume of liquid required for colon cleansing (using two bottles) is 3 quarts. The following are recommended dosage and administration instructions for adults:

Dose 1 – On the Day Prior to Colonoscopy:

- May consume a light breakfast, or only clear liquids (no solid food).
- In the evening before the procedure, pour the contents of one bottle of sodium sulfate, potassium sulfate, and magnesium sulfate oral solution into the mixing container provided.
- Add cool drinking water to the 16-ounce fill line on the container, mix, and drink the entire amount.
- Drink two additional containers filled with water to the 16-ounce fill line over the next hour.

Dose 2 - Day of Colonoscopy:

- Continue to consume only clear liquids.
- In the morning (10 hours to 12 hours after the evening dose) on the day of the procedure, pour the contents of the second bottle of sodium sulfate, potassium sulfate, and magnesium sulfate oral solution into the mixing container provided.
- Add cool drinking water to the 16-ounce fill line on the container, mix, and drink the entire amount.
- Drink two additional containers filled with water to the 16-ounce fill line over the next hour.
- Complete all solution of sodium sulfate, potassium sulfate, and magnesium sulfate oral solution and required water at least two hours prior to colonoscopy.

3 DOSAGE FORMS AND STRENGTHS

Sodium sulfate, potassium sulfate, and magnesium sulfate oral solution (for adults):Two bottles each containing 6 ounces of an oral solution of 17.5 grams sodium sulfate, USP, 3.13 grams potassium sulfate, and 1.6 grams magnesium sulfate, USP as a clear to slightly hazy liquid.

When diluted as directed, the solution is clear and colorless.

Pediatric use information is approved for Braintree Laboratories, Inc.'s SUPREP BOWEL PREP KIT (sodium sulfate, potassium sulfate, and magnesium sulfate) oral solution. However, due to Braintree Laboratories, Inc.'s marketing exclusivity rights, this drug product is not labeled with that pediatric information.

4 CONTRAINDICATIONS

Sodium sulfate, potassium sulfate, and magnesium sulfate oral solution is contraindicated in the following conditions:

- Gastrointestinal obstruction or ileus [see Warnings and Precautions (5.6)]
- Bowel perforation [see Warnings and Precaution (5.6)]
- Toxic colitis or toxic megacolon
- Gastric retention
- Hypersensitivity to any of the ingredients in sodium sulfate, potassium sulfate, and magnesium sulfate oral solution

5 WARNINGS AND PRECAUTIONS

5.1 Serious Fluid and Serum Chemistry Abnormalities

Advise all patients to hydrate adequately before, during, and after the use of sodium sulfate, potassium sulfate, and magnesium sulfate oral solution. If a patient develops significant vomiting or signs of dehydration after taking sodium sulfate, potassium sulfate, and magnesium sulfate oral solution, consider performing post-colonoscopy lab tests (electrolytes, creatinine, and BUN).

Fluid and electrolyte disturbances can lead to serious adverse events including cardiac arrhythmias, seizures and renal impairment. Correct fluid and electrolyte abnormalities before treatment with sodium sulfate, potassium sulfate, and magnesium sulfate oral solution. Use sodium sulfate, potassium sulfate, and magnesium sulfate oral solution with caution in patients with conditions, or who are using medications, that increase the risk for fluid and electrolyte disturbances or may increase the risk of adverse events of seizure, arrhythmias, and renal impairment [see Drug Interactions (7.1)] .

Sodium sulfate, potassium sulfate, and magnesium sulfate oral solution can cause temporary elevations in uric acid [see Adverse Reactions (6.1)] . Uric acid fluctuations in patients with gout may precipitate an acute flare. The potential for uric acid elevation should be considered before administering sodium sulfate, potassium sulfate, and magnesium sulfate oral solution to patients with gout or other disorders of uric acid metabolism.

5.2 Cardiac Arrhythmias

There have been rare reports of serious arrhythmias associated with the use of ionic osmotic laxative products for bowel preparation. Use caution when prescribing sodium sulfate, potassium sulfate, and magnesium sulfate oral solution for patients at increased risk of arrhythmias (e.g., patients with a history of prolonged QT, uncontrolled arrhythmias, recent myocardial infarction, unstable angina, congestive heart failure, or cardiomyopathy). Consider pre-dose and post-colonoscopy ECGs in patients at increased risk of serious cardiac arrhythmias.

5.3 Seizures

There have been reports of generalized tonic-clonic seizures and/or loss of consciousness associated with use of bowel preparation products in patients with no prior history of seizures. The seizure cases were associated with electrolyte abnormalities (e.g., hyponatremia, hypokalemia, hypocalcemia, and hypomagnesemia) and low serum osmolality. The neurologic abnormalities resolved with correction of fluid and electrolyte abnormalities.

Use caution when prescribing sodium sulfate, potassium sulfate, and magnesium sulfate oral solution for patients with a history of seizures and in patients at increased risk of seizure, such as patients taking medications that lower the seizure threshold (e.g., tricyclic antidepressants), patients withdrawing from alcohol or benzodiazepines, or patients with known or suspected hyponatremia [see Drug Interactions (7.1)] .

5.4 Use in Patients with Risk of Renal Injury

Use sodium sulfate, potassium sulfate, and magnesium sulfate oral solution with caution in patients with impaired renal function or patients taking concomitant medications that may affect renal function (such as diuretics, angiotensin converting enzyme inhibitors, angiotensin receptor blockers, or non-steroidal anti-inflammatory drugs) [see Drug Interactions (7.1)] . These patients may be at risk for renal injury. Advise these patients of the importance of adequate hydration with sodium sulfate, potassium sulfate, and magnesium sulfate oral solution and consider performing baseline and post-colonoscopy laboratory tests (electrolytes, creatinine, and BUN) in these patients [see Use in Specific Populations (8.6)] .

5.5 Colonic Mucosal Ulcerations and Ischemic Colitis

Osmotic laxative products may produce colonic mucosal aphthous ulcerations, and there have been reports of more serious cases of ischemic colitis requiring hospitalization. Concurrent use of stimulant laxatives and sodium sulfate, potassium sulfate, and magnesium sulfate oral solution may increase these risks [see Drug Interactions (7.3)] . Consider the potential for mucosal ulcerations resulting from the bowel preparation when interpreting colonoscopy findings in patients with known or suspect inflammatory bowel disease (IBD).

5.6 Use in Patients with Significant Gastrointestinal Disease

If gastrointestinal obstruction or perforation is suspected, perform appropriate diagnostic studies to rule out these conditions before administering sodium sulfate, potassium sulfate, and magnesium sulfate oral solution [see Contraindications (4)] .

Use with caution in patients with severe active ulcerative colitis.

5.7 Aspiration

Patients with impaired gag reflex or other swallowing abnormalities are at risk for regurgitation or aspiration of sodium sulfate, potassium sulfate, and magnesium sulfate oral solution. Observe these patients during administration of sodium sulfate, potassium sulfate, and magnesium sulfate oral solution. Use with caution in these patients.

6 ADVERSE REACTIONS

The following important adverse reactions for bowel preparations are described elsewhere in the labeling:

- Serious Fluid and Serum Chemistry Abnormalities [see Warnings and Precautions (5.1)]
- Cardiac Arrhythmias [see Warnings and Precautions (5.2)]
- Seizures [see Warnings and Precautions (5.3)]
- Use in Patients with Risk of Renal Injury [see Warnings and Precautions (5.4)]
- Colonic Mucosal Ulceration and Ischemic Colitis [see Warnings and Precautions (5.5)]
- Patients with Significant Gastrointestinal Disease [see Warnings and Precautions (5.6)]
- Aspiration [see Warnings and Precautions (5.7)]

6.1 Clinical Trials Experience

Because clinical studies are conducted under widely varying conditions, adverse reaction rates observed in the clinical studies of a drug cannot be directly compared to rates in clinical studies of another drug and may not reflect the rates observed in practice.

Adults

The safety of sodium sulfate, potassium sulfate, and magnesium sulfate oral solution was evaluated in a multi-center, randomized, active controlled trial in 379 adult patients undergoing colonoscopy [see Clinical Studies (14)] .

Most Common Adverse Reactions

Table 1 shows the most common adverse reactions reported in at least 2% of patients receiving sodium sulfate, potassium sulfate, and magnesium sulfate oral solution or the control (a bowel prep containing polyethylene glycol and electrolytes (PEG + E)) administered in split-dose (2-day) regimens.

Table 1: Common Adverse Reactions [reported in at least 2% of patients] in Adult Patients Undergoing Colonoscopy in a Randomized, Active Controlled Trial
 | Split-Dose (2-Day) Regimen
Symptom | Sodium Sulfate, Potassium Sulfate, and Magnesium Sulfate Oral Solution Product % N = 190 | PEG + E Product % N = 189
Overall Discomfort | 54 | 67
Abdominal Distension | 40 | 52
Abdominal Pain | 36 | 43
Nausea | 36 | 33
Vomiting | 8 | 4

Laboratory Abnormalities

Table 2 shows the most common laboratory abnormalities (at least 10% in either treatment group and more than 2% difference between groups) for patients who developed new abnormalities of important electrolytes and uric acid after completing the bowel preparation with either sodium sulfate, potassium sulfate, and magnesium sulfate oral solution or PEG+E administered as a split-dose (2-day) regimen.

Table 2: Adult Patients with Normal Baseline Serum Chemistry with A Shift to an Abnormal Value While on the Split-Dose (2-Day) Regimen [The study was not designed to support comparative claims for the laboratory abnormalities reported in this table.]
 |  | Day of Colonoscopy N (%) [Percent (n/N) of patients where N = number of patients with normal baseline who had abnormal values at the timepoint(s) of interest.] | Day 30 N (%)†
Bicarbonate (low) | Sodium sulfate, potassium sulfate, and magnesium sulfate oral solution | 20 (13) | 7 (4)
 | PEG + Electrolytes | 24 (15) | 4 (3)
Bilirubin, total (high) | Sodium sulfate, potassium sulfate, and magnesium sulfate oral solution | 14 (9) | 0 (0)
 | PEG + Electrolytes | 20 (12) | 3 (2)
BUN (high) | Sodium sulfate, potassium sulfate, and magnesium sulfate oral solution | 2 (2) | 14 (11)
 | PEG + Electrolytes | 4 (3) | 19 (15)
Calcium (high) | Sodium sulfate, potassium sulfate, and magnesium sulfate oral solution | 16 (10) | 8 (5)
 | PEG + Electrolytes | 6 (4) | 6 (4)
Chloride (high) | Sodium sulfate, potassium sulfate, and magnesium sulfate oral solution | 4 (2) | 6 (4)
 | PEG + Electrolytes | 20 (12) | 6 (4)
Osmolality (high) | Sodium sulfate, potassium sulfate, and magnesium sulfate oral solution | 8 (6) | NA
 | PEG + Electrolytes | 19 (13) | NA
Uric acid (high) | Sodium sulfate, potassium sulfate, and magnesium sulfate oral solution | 27 (24) | 13 (12)
 | PEG + Electrolytes | 12 (10) | 20 (17)

Less Common Adverse Reactions

AV Block (1 case) and CK increase.

Adverse Reactions with Unapproved Use

In another study of 408 adult patients, higher rates of the following adverse reactions and laboratory abnormalities were reported in patients treated with sodium sulfate, potassium sulfate, and magnesium sulfate oral solution as an evening-only (1-day) regimen compared to the split-dose (2-day) regimen.

- overall discomfort, abdominal distention, nausea, and vomiting
- total bilirubin (high), BUN (high), creatinine (high), osmolality (high), potassium (high) and uric acid (high)

Administration of sodium sulfate, potassium sulfate, and magnesium sulfate oral solution in an evening-only (1-day) dosing regimen is not recommended.

Pediatric use information is approved for Braintree Laboratories, Inc.'s SUPREP BOWEL PREP KIT (sodium sulfate, potassium sulfate, and magnesium sulfate) oral solution. However, due to Braintree Laboratories, Inc.'s marketing exclusivity rights, this drug product is not labeled with that pediatric information.

7 DRUG INTERACTIONS

7.1 Drugs That May Increase Risks of Fluid and Electrolyte Abnormalities

Use caution when prescribing sodium sulfate, potassium sulfate, and magnesium sulfate oral solution to patients taking medications that increase the risk of fluid and electrolyte disturbances or may increase the risk of adverse events of seizure, arrhythmias, and prolonged QT in the setting of fluid and electrolyte abnormalities [see Warnings and Precautions (5.1, 5.2, 5.3, 5.4)] .

7.2 Potential for Reduced Drug Absorption

Sodium sulfate, potassium sulfate, and magnesium sulfate oral solution can reduce the absorption of other co-administered drugs [see Dosage and Administration (2.1)] .

- Administer oral medications at least one hour before starting each dose of sodium sulfate, potassium sulfate, and magnesium sulfate oral solution.
- Administer tetracycline and fluoroquinolone antibiotics, iron, digoxin, chlorpromazine, and penicillamine at least 2 hours before and not less than 6 hours after administration of sodium sulfate, potassium sulfate, and magnesium sulfate oral solution to avoid chelation with magnesium.

7.3 Stimulant Laxatives

Concurrent use of stimulant laxatives and sodium sulfate, potassium sulfate, and magnesium sulfate oral solution may increase the risk of mucosal ulceration or ischemic colitis. Avoid use of stimulant laxatives (e.g., bisacodyl, sodium picosulfate) while taking sodium sulfate, potassium sulfate, and magnesium sulfate oral solution [see Warnings and Precautions (5.5)] .

8 USE IN SPECIFIC POPULATIONS

8.1 Pregnancy

Risk Summary

There are no available data on sodium sulfate, potassium sulfate, and magnesium sulfate oral solution use in pregnant women to evaluate for a drug-associated risk of major birth defects, miscarriage, or adverse maternal or fetal outcomes. Animal reproductive studies have not been conducted with sodium sulfate, potassium sulfate, and magnesium sulfate (Sodium sulfate, potassium sulfate, and magnesium sulfate oral solution).

The estimated background risk of major birth defects and miscarriage for the indicated population is unknown. All pregnancies have a background risk of birth defect, loss, or other adverse outcomes. In the U.S. general population, the estimated background risk of major birth defects and miscarriage in clinically recognized pregnancies is 2% to 4% and 15% to 20%, respectively.

8.2 Lactation

Risk Summary

There are no data available data on the presence of sodium sulfate, potassium sulfate, and magnesium sulfate oral solution in human or animal milk, the effects on the breastfed child, or the effects on milk production. The developmental and health benefits of breastfeeding should be considered along with the mother's clinical need for sodium sulfate, potassium sulfate, and magnesium sulfate oral solution and any potential adverse effects on the breastfed child from sodium sulfate, potassium sulfate, and magnesium sulfate oral solution or from the underlying maternal condition.

8.4 Pediatric Use

The safety and effectiveness of sodium sulfate, potassium sulfate, and magnesium sulfate oral solution in pediatric patients less than 12 years of age have not been established.

Pediatric use information is approved for Braintree Laboratories, Inc.'s SUPREP BOWEL PREP KIT (sodium sulfate, potassium sulfate, and magnesium sulfate) oral solution. However, due to Braintree Laboratories, Inc.'s marketing exclusivity rights, this drug product is not labeled with that pediatric information.

8.5 Geriatric Use

Of the 375 patients who received sodium sulfate, potassium sulfate, and magnesium sulfate oral solution in clinical trials, 94 (25%) were 65 years of age or older, and 25 (7%) were 75 years of age or older. No overall differences in safety or effectiveness of sodium sulfate, potassium sulfate, and magnesium sulfate oral solution, administered as the recommended split-dose (2-day) regimen, were observed between geriatric patients and younger patients. Geriatric patients reported more vomiting when sodium sulfate, potassium sulfate, and magnesium sulfate oral solution was given as a one-day preparation (not a recommended regimen). Elderly patients are more likely to have decreased hepatic, renal or cardiac function and may be more susceptible to adverse reactions resulting from fluid and electrolyte abnormalities [see Warnings and Precautions (5.1)].

8.6 Renal Impairment

Use sodium sulfate, potassium sulfate, and magnesium sulfate oral solution with caution in patients with renal impairment or patients taking concomitant medications that may affect renal function. These patients may be at risk for renal injury. Advise these patients of the importance of adequate hydration before, during and after use of sodium sulfate, potassium sulfate, and magnesium sulfate oral solution and consider performing baseline and post-colonoscopy laboratory tests (electrolytes, creatinine, and BUN) in these patients [see Warnings and Precautions (5.4)] .

10 OVERDOSAGE

Overdosage of more than the recommended dose of sodium sulfate, potassium sulfate, and magnesium sulfate oral solution may lead to severe electrolyte disturbances, as well as dehydration and hypovolemia, with signs and symptoms of these disturbances. [see Warnings and Precautions (5.1, 5.2, 5.3)] . Monitor for fluid and electrolyte disturbances and treat symptomatically.

11 DESCRIPTION

Sodium sulfate, potassium sulfate, and magnesium sulfate oral solution (for adults)is an osmotic laxative and is provided as two bottles each containing 6 ounces of solution.

Each bottle contains: 17.5 grams sodium sulfate, USP, 3.13 grams potassium sulfate, and 1.6 grams magnesium sulfate, USP. Inactive ingredients include: citric acid anhydrous, malic acid, natural and artificial blueberry flavor, purified water, sodium benzoate, and sucralose.

Sodium Sulfate, USP

The chemical name is Na2SO4. The average molecular weight is 142.04 g/mol. The structural formula is:

Potassium Sulfate, FCC, purified

The chemical name is K2SO4. The average molecular weight is 174.26 g/mol. The structural formula is:

Magnesium Sulfate, USP

The chemical name is MgSO4. The average molecular weight: 120.37 g/mol. The structural formula is:

Each sodium sulfate, potassium sulfate, and magnesium sulfate oral solution kit also contains a high density polyethylene (HDPE) mixing container.

Pediatric use information is approved for Braintree Laboratories, Inc.’s SUPREP BOWEL PREP KIT (sodium sulfate, potassium sulfate, and magnesium sulfate) oral solution. However, due to Braintree Laboratories, Inc.’s marketing exclusivity rights, this drug product is not labeled with that pediatric information.

12 CLINICAL PHARMACOLOGY

12.1 Mechanism of Action

Sulfate salts provide sulfate anions, which are poorly absorbed. The osmotic effect of unabsorbed sulfate anions and the associated cations causes water to be retained within the gastrointestinal tract.

12.2 Pharmacodynamics

No formal pharmacodynamic studies have been conducted with sodium sulfate, potassium sulfate, and magnesium sulfate oral solution.

12.3 Pharmacokinetics

Absorption and Elimination

After administration of sodium sulfate, potassium sulfate, and magnesium sulfate oral solution in six healthy subjects, the time at which serum sulfate reached its highest point (Tmax) was approximately 17 hours after the first dose or approximately 5 hours after the second dose, and then declined with a half-life of 8.5 hours.

Excretion

Fecal excretion was the primary route of sulfate elimination.

Specific Populations

Patients with Renal Impairment

The disposition of sulfate after ingestion of sodium sulfate, potassium sulfate, and magnesium sulfate oral solution was studied in patients (N = 6) with moderate renal impairment (creatinine clearance of 30 mL/min to 49 mL/min). In patients with moderate renal impairment, mean AUC was 54% higher and mean Cmaxwas 44% higher, than healthy subjects.

The mean sulfate concentrations in healthy subjects and in patients with moderate renal impairment returned to their respective baselines by Day 6 after dose initiation. Urinary excretion of sulfate over 30 hours after the first dose was approximately 16% lower in patients with moderate renal impairment than in healthy subjects. These differences are not considered clinically meaningful.

Patients with Hepatic Impairment

The disposition of sulfate after ingestion of sodium sulfate, potassium sulfate, and magnesium sulfate oral solution was studied in patients (N = 6) with mild to moderate hepatic impairment (Child-Pugh grades A and B). Systemic exposure of serum sulfate (AUC and Cmax) was similar between healthy subjects and patients with hepatic impairment. The mean sulfate concentrations in healthy subjects and in patients with mild to moderate hepatic impairment returned to their respective baselines by Day 6 after dose initiation. Urinary excretion of sulfate over 30 hours after the first dose was similar between patients with hepatic impairment and healthy subjects.

13 NONCLINICAL TOXICOLOGY

13.2 Animal Toxicology and/or Pharmacology

The sulfate salts of sodium, potassium, and magnesium contained in sodium sulfate, potassium sulfate, and magnesium sulfate oral solution were administered orally (gavage) to rats and dogs up to 28 days up to a maximum daily dose of 5 grams/kg/day (approximately 0.9 time and 3 times for rats and dogs, respectively, the recommended human dose of 44 grams/day or 0.89 grams/kg based on the body surface area). In rats, the sulfate salts caused diarrhea and electrolyte and metabolic changes, including hypochloremia, hypokalemia, hyponatremia, lower serum osmolality, and high serum bicarbonate. Significant renal changes included increased fractional sodium excretion, increased urinary sodium and potassium excretion, and alkaline urine in both males and females. In addition, creatinine clearance was significantly decreased in females at the highest dose. No microscopic renal changes were seen. In dogs, the sulfate salts caused emesis, excessive salivation, excessive drinking of water, and abnormal excreta (soft and/or mucoid feces and/or diarrhea) and increased urine pH and sodium excretion.

14 CLINICAL STUDIES

Adults

The colon cleansing efficacy of sodium sulfate, potassium sulfate, and magnesium sulfate oral solution was evaluated in a randomized, single-blind, active-controlled, multicenter study in adult patients scheduled to have a colonoscopy. There were 363 adult patients included in the efficacy analysis. Patients ranged in age from 20 years to 84 years (mean age 55 years) and 54% were female. Race distribution was 86% Caucasian, 9% African-American, and 5% other.

Patients were randomized to one of the following two colon preparation regimens: sodium sulfate, potassium sulfate, and magnesium sulfate oral solution or a marketed polyethylene glycol (PEG) plus electrolytes bowel preparation. In the Study sodium sulfate, potassium sulfate, and magnesium sulfate oral solution was administered as a split-dose (two-day) regimen. The PEG bowel prep was also given as a split-dose preparation according to its labeled instructions. Patients receiving sodium sulfate, potassium sulfate, and magnesium sulfate oral solution were limited to a light breakfast followed by clear liquids on the day prior to the day of colonoscopy; patients receiving the PEG bowel prep were allowed to have a normal breakfast and a light lunch, followed by clear liquids.

The primary efficacy endpoint was the proportion of patients with successful colon cleansing as assessed by the colonoscopists, who were not informed about the type of preparation received, as shown in Table 3. In the study, no clinically or statistically significant differences were seen between the group treated with sodium sulfate, potassium sulfate, and magnesium sulfate oral solution and the group treated with the PEG bowel prep.

Table 3: Proportion of Adult Patients with Successful Colon Cleansing Response Rates
Treatment Group | Regimen | N | Responders [Responders were patients whose colon preparations were graded excellent (no more than small bits of adherent feces/fluid) or good (small amounts of feces or fluid not interfering with the exam) by the colonoscopist.] % (95% C. I.) | Sodium Sulfate, Potassium Sulfate, and Magnesium Sulfate Oral Solution - PEG Difference (95% CI)
Sodium sulfate, potassium sulfate, and magnesium sulfate oral solution (with light breakfast) | Split-Dose | 180 | 97% (94%, 99%)
PEG bowel prep (with normal breakfast & light lunch) | Split-Dose | 183 | 96% (92%, 98%) | 2% [Does not equal difference in tabled responder rates due to rounding effects.] (-2%, 5%)

Pediatric use information is approved for Braintree Laboratories, Inc.'s SUPREP BOWEL PREP KIT (sodium sulfate, potassium sulfate, and magnesium sulfate) oral solution. However, due to Braintree Laboratories, Inc.'s marketing exclusivity rights, this drug product is not labeled with that pediatric information.

16 HOW SUPPLIED/STORAGE AND HANDLING

Each sodium sulfate, potassium sulfate, and magnesium sulfate oral solution kit (for adults)(NDC 69452-428-62) contains:

- Two bottles each containing 6-ounces of an oral solution of 17.5 grams sodium sulfate, USP, 3.13 grams potassium sulfate, and 1.6 grams magnesium sulfate, USP as a clear to slightly hazy liquid. When diluted as directed, the solution is clear and colorless.
- One (1) 20-ounce mixing container with a 16-ounce fill line.

STORAGE AND HANDLING

Store at 20°C to 25°C (68°F to 77°F). Excursions permitted between 15°C to 30°C (59°F to 86°F) [See USP controlled room temperature].

Keep out of reach of children.

Pediatric use information is approved for Braintree Laboratories, Inc.'s SUPREP BOWEL PREP KIT (sodium sulfate, potassium sulfate, and magnesium sulfate) oral solution. However, due to Braintree Laboratories, Inc.'s marketing exclusivity rights, this drug product is not labeled with that pediatric information.

17 PATIENT COUNSELING INFORMATION

Advise the patient and/or caregiver to read the FDA-approved patient labeling (Medication Guide).

Instruct patients or caregivers:

- Must dilute sodium sulfate, potassium sulfate, and magnesium sulfate oral solution before ingestion.
- Must consume additional water after each dose of sodium sulfate, potassium sulfate, and magnesium sulfate oral solution.
- On the day before colonoscopy, consume only a light breakfast or clear liquids (e.g., water, apple or orange juice without pulp, lemonade, coffee, tea, or chicken broth). On the day of the colonoscopy only consume clear liquids up to two hours prior to colonoscopy.
- Two doses of sodium sulfate, potassium sulfate, and magnesium sulfate oral solution are required for a complete preparation for colonoscopy .One bottle of sodium sulfate, potassium sulfate, and magnesium sulfate oral solution is equivalent to one dose.
- Do not take other laxatives while taking sodium sulfate, potassium sulfate, and magnesium sulfate oral solution.
- Do not eat solid food or drink milk or eat or drink anything colored red or purple.
- Do not drink alcohol.
- Do not take oral medications within one hour of starting each dose of sodium sulfate, potassium sulfate, and magnesium sulfate oral solution.
- If taking tetracycline or fluoroquinolone antibiotics, iron, digoxin, chlorpromazine, or penicillamine, take these medications at least 2 hours before and not less than 6 hours after administration of sodium sulfate, potassium sulfate, and magnesium sulfate oral solution [see Drug Interactions (7.2)] .
- Stop consumption of all fluids at least 2 hours prior to colonoscopy.
- Contact their healthcare provider if they develop significant vomiting or signs of dehydration after taking sodium sulfate, potassium sulfate, and magnesium sulfate oral solution or if they experience cardiac arrhythmias or seizures [see Warnings and Precautions (5.1, 5.2, 5.3)] .

Distributed by:
Bionpharma Inc.
Princeton, NJ 08540 USA

Rev. 1/2025

For India Manufacturing Site:

Distributed by:
Bionpharma Inc.
Princeton, NJ 08540 USA
Rev. 6/2025
MADE IN INDIA
948026883

MEDICATION GUIDE
Sodium Sulfate, Potassium Sulfate, and Magnesium Sulfate Oral Solution
(SO-dee-uhm sul-fāt, puh-TAS-ee-uhm sul-fāt and mag-NEE-zee-uhm sul-fāt)

Read and understand this Medication Guide instructions at least 2 days beforeyour colonoscopy and again before you start taking sodium sulfate, potassium sulfate, and magnesium sulfate oral solution.

What is the most important information I should know about sodium sulfate, potassium sulfate, and magnesium sulfate oral solution?
Sodium sulfate, potassium sulfate, and magnesium sulfate oral solution and other bowel preparations can cause serious side effects, including:

- Serious loss of body fluid (dehydration) and changes in blood salts (electrolytes) in your blood. These changes can cause:
- abnormal heartbeats that can cause death.
- seizures. This can happen even if you have never had a seizure.
- kidney problems

Your chance of having fluid loss and changes in body salts with sodium sulfate, potassium sulfate, and magnesium sulfate oral solution is higher if you:

- have heart problems
- have kidney problems
- take water pills or non-steroidal anti-inflammatory drugs (NSAIDS)

Tell your healthcare provider right away if you have any of these symptoms of a loss of too much body fluid (dehydration) while taking sodium sulfate, potassium sulfate, and magnesium sulfate oral solution:

- vomiting
- dizziness

- urinating less often than normal
- headache

See " What are the possible side effects of sodium sulfate, potassium sulfate, and magnesium sulfate oral solution?" for more information about side effects.

What is sodium sulfate, potassium sulfate, and magnesium sulfate oral solution?
Sodium sulfate, potassium sulfate, and magnesium sulfate oral solution is a prescription medicine used by adults to clean the colon before a colonoscopy. Sodium sulfate, potassium sulfate, and magnesium sulfate oral solution cleans your colon by causing you to have diarrhea. Cleaning your colon helps your healthcare provider see the inside of your colon more clearly during your colonoscopy.
It is not known if sodium sulfate, potassium sulfate, and magnesium sulfate oral solution is safe and effective in children under 12 years of age.

Do nottake sodium sulfate, potassium sulfate, and magnesium sulfate oral solution if your healthcare provider has told you that you have:

- a blockage in your intestine (bowel (obstruction)
- an opening in the wall of your stomach or intestine (bowel perforation)
- a very dilated intestine (toxic megacolon)
- problems with the emptying of food and fluid from your stomach (gastric retention)
- an allergy to any of the ingredients in sodium sulfate, potassium sulfate, and magnesium sulfate oral solution. See the end of this Medication Guide for a complete list of ingredients in sodium sulfate, potassium sulfate, and magnesium sulfate oral solution.

Before taking sodium sulfate, potassium sulfate, and magnesium sulfate oral solution, tell your healthcare provider about all of your medical conditions, including if you:

- have problems with serious loss of body fluid (dehydration) and changes in blood salts (electrolytes).
- have gout
- have heart problems including an irregular heartbeat, especially a condition called "QT prolongation".
- have a history of seizures or take medicines for seizures.
- are withdrawing from drinking alcohol or from taking benzodiazepines.
- have a low blood salt (sodium) level.
- have kidney problems or take medicines for kidney problems.
- have stomach or bowel problems including ulcerative colitis.
- have problems with swallowing or gastric reflux.
- are pregnant or plan to become pregnant. It is not known if sodium sulfate, potassium sulfate, and magnesium sulfate oral solution will harm your unborn baby. Talk to your healthcare provider if you are pregnant.
- are breastfeeding or plan to breastfeed. It is not known if sodium sulfate, potassium sulfate, and magnesium sulfate oral solution passes into your breast milk. You and your healthcare provider should decide if you will take sodium sulfate, potassium sulfate, and magnesium sulfate oral solution while breastfeeding.

Tell your healthcare provider about all the medicines you take,including prescription and over-the-counter medicines, vitamins, and herbal supplements.
Sodium sulfate, potassium sulfate, and magnesium sulfate oral solution may affect how other medicines work. Medicines taken by mouth may not be absorbed properly when taken within 1 hour before the start of each dose of sodium sulfate, potassium sulfate, and magnesium sulfate oral solution.
Especially tell your healthcare provider if you take:

- medicines for blood pressure or heart problems.
- medicines for kidney problems.
- medicines for seizures.
- water pills (diuretics).
- non-steroidal anti-inflammatory medicines (pain medicines).
- medicines for depression or mental health problems.
- laxatives. Do nottake other laxatives while taking sodium sulfate, potassium sulfate, and magnesium sulfate oral solution.

The following medicines should be taken at least 2 hours before starting sodium sulfate, potassium sulfate, and magnesium sulfate oral solution and not less than 6 hours after taking sodium sulfate, potassium sulfate, and magnesium sulfate oral solution:

- tetracycline
- fluoroquinolone antibiotics
- iron
- digoxin (Lanoxin)
- chlorpromazine
- penicillamine (Cuprimine, Depen)

Ask your healthcare provider or pharmacist for a list of these medicines if you are not sure if you are taking any of the medicines listed above.
Know the medicines you take. Keep a list of them to show your healthcare provider and pharmacist when you get a new medicine.

How should I take sodium sulfate, potassium sulfate, and magnesium sulfate oral solution?
See the Instructions for Usein the Patient Instructions for Use Booklet for dosing instructions. You must read, understand, and follow these instructions to take sodium sulfate, potassium sulfate, and magnesium sulfate oral solution the right way.

- Take sodium sulfate, potassium sulfate, and magnesium sulfate oral solution exactly as your healthcare provider tells you to take it.
- Each bottle of sodium sulfate, potassium sulfate, and magnesium sulfate oral solution must be mixed with water (diluted) before drinking.
- It is important for you to drink the additional prescribed amount of water listed in the Instructions for Use to prevent fluid loss (dehydration).
- One bottle of sodium sulfate, potassium sulfate, and magnesium sulfate oral solution is equal to one dose.
- Two doses of sodium sulfate, potassium sulfate, and magnesium sulfate oral solution are required for complete colonoscopy preparation.
- All people taking sodium sulfate, potassium sulfate, and magnesium sulfate oral solution should follow these general instructions starting 1 day beforeyour colonoscopy:
  - eat only a light breakfast or clear liquids (for example: water, strained fruit juice without pulp, lemonade, plain coffee, or tea, chicken broth, gelatin dessert without fruit) on the day before your procedure.
  - only drink clear liquids the rest of the day and the next day until 2 hours before your colonoscopy. Stopdrinking all fluids at least 2 hours before your colonoscopy.
  - after taking sodium sulfate, potassium sulfate, and magnesium sulfate oral solution if you have any bloating or feeling like your stomach is upset, wait to take your second dose until your stomach feels better.
- While taking sodium sulfate, potassium sulfate, and magnesium sulfate oral solution, do not:
  - take any other laxatives.
  - take any medicines by mouth (oral) within 1 hour of starting sodium sulfate, potassium sulfate, and magnesium sulfate oral solution.
  - eat solid foods, drink dairy (such as milk), or drink alcohol while taking sodium sulfate, potassium sulfate, and magnesium sulfate oral solution and until after your colonoscopy.
  - eat or drink anything colored red or purple.

Contact your healthcare provider right awayif after taking sodium sulfate, potassium sulfate, and magnesium sulfate oral solution you have severe vomiting, signs of dehydration, changes in consciousness such as feeling confused, delirious or fainting (loss of consciousness) or seizures after taking sodium sulfate, potassium sulfate, and magnesium sulfate oral solution.

What are the possible side effects of sodium sulfate, potassium sulfate, and magnesium sulfate oral solution?
Sodium sulfate, potassium sulfate, and magnesium sulfate oral solution can cause serious side effects, including:

- See " What is the most important information I should know about sodium sulfate, potassium sulfate, and magnesium sulfate oral solution?"
- Changes in certain blood tests. Your healthcare provider may do blood tests after you take sodium sulfate, potassium sulfate, and magnesium sulfate oral solution to check your blood for changes. Tell your healthcare provider if you have any symptoms of too much fluid loss, including:

- vomiting
- dizziness
- urinate less than usual
- seizures

- nausea
- stomach area (abdomen) cramping
- trouble drinking clear liquid
- heart problems

- bloating
- headache
- trouble swallowing
- worsening gout

- Ulcers of the bowel or bowel problems (ischemic colitis).Tell your healthcare provider right away if you have severe stomach-area (abdomen) pain or rectal bleeding.

The most common side effects of sodium sulfate, potassium sulfate, and magnesium sulfate oral solution in adults include:

- overall discomfort
- stomach pain
- vomiting

- stomach bloating
- nausea

These are not all the possible side effects of sodium sulfate, potassium sulfate, and magnesium sulfate oral solution.
Call your doctor for medical advice about side effects. You may report side effects to FDA at 1-800-FDA-1088.

How should I store sodium sulfate, potassium sulfate, and magnesium sulfate oral solution?

- Store sodium sulfate, potassium sulfate, and magnesium sulfate oral solution at room temperature, between 68°F to 77°F (20°C to 25°C).

Keep sodium sulfate, potassium sulfate, and magnesium sulfate oral solution and all medicines out of the reach of children.

General information about the safe and effective use of sodium sulfate, potassium sulfate, and magnesium sulfate oral solution.
Medicines are sometimes prescribed for purposes other than those listed in a Medication Guide. Do not use sodium sulfate, potassium sulfate, and magnesium sulfate oral solution for a condition for which it was not prescribed. Do not give sodium sulfate, potassium sulfate, and magnesium sulfate oral solution to other people, even if they are going to have the same procedure you are. It may harm them. You can ask your pharmacist or healthcare provider for information about sodium sulfate, potassium sulfate, and magnesium sulfate oral solution that is written for healthcare professionals.

For more information, call 1-888-235-BION or 1-888235-2466.

What are the ingredients in sodium sulfate, potassium sulfate, and magnesium sulfate oral solution?
Sodium sulfate, potassium sulfate, and magnesium sulfate oral solution is supplied in one dosage strength. Sodium sulfate, potassium sulfate, and magnesium sulfate oral solution comes in a carton containing two 6-ounce bottles, along with a 20-ounce polyethylene mixing container.
Each bottle contains:
Active ingredients:sodium sulfate, potassium sulfate, and magnesium sulfate.
Inactive ingredients:citric acid anhydrous, malic acid, natural and artificial blueberry flavor, purified water, sodium benzoate, and sucralose.
Pediatric use information is approved for Braintree Laboratories, Inc.'s SUPREP BOWEL PREP KIT (sodium sulfate, potassium sulfate, and magnesium sulfate) oral solution. However, due to Braintree Laboratories, Inc.'s marketing exclusivity rights, this drug product is not labeled with that pediatric information.

Distributed by:
Bionpharma Inc.
Princeton, NJ 08540 USA
This Medication Guide has been approved by the U.S. Food and Drug Administration. Revised 1/2025

For India Manufacturing Site:

Distributed by: Bionpharma Inc.
Princeton, NJ 08540 USA
MADE IN INDIA

This Medication Guide has been approved by the U.S. Food and Drug Administration. Rev. 6/2025

Instructions for Use

On the day before your procedure
• You may have a light breakfast or have clear liquids ONLY; please have nothing for dinner
• DO NOTdrink milk
• DO NOTeat or drink anything colored red or purple
• DO NOTdrink alcoholic beverages
Any of the following clear liquids are OK
Water
Strained fruit juices (without pulp) including apple, orange, white grape, or white cranberry
Limeade or lemonade
Coffee or tea (DO NOTuse any dairy or non-dairy creamer)
Chicken broth
Gelatin desserts without added fruit or topping (NO RED OR PURPLE)

Your doctor has recommended split-dose sodium sulfate, potassium sulfate, and magnesium sulfate oral solution
(Both 6-ounce bottles are required for a complete prep.)

Split-Dose (2-Day) Regimen

- On the evening before procedure (or when your doctor tells you to begin) complete steps 1 through 4 using one (1) 6-ounce bottle before going to bed
- On the morning of your procedure, repeat steps 1 through 4 using the other 6-ounce bottle

Pour ONE(1) 6-ounce bottle of prep liquid into the mixing container.

Add cool drinking water to the 16-ounce line on the container and mix.

Drink ALL the liquid in the container.

You mustdrink two (2) more 16-ounce containers of water over the next 1 hour.

NOTE:Dilute the solution concentrate as directed prior to use.
NOTE: You mustfinish drinking the final glass of water at least 2 hours, or as directed, before your colonoscopy.

PRINCIPAL DISPLAY PANEL - Label

NDC 69452-428-97

Sodium Sulfate, Potassium Sulfate, and Magsium Sulfate Oral Solution

For Adults

(17.5g/3.13g/1.6g) per 6 ounces

Dispense the enclosed Medication Guide to each patient.

Rx only

This bottle contains 6 ounces (177 mL) of liquid bowel prep

For India Manufacturing site:

PRINCIPAL DISPLAY PANEL - Carton

NDC 69452-428-62

Sodium Sulfate, Potassium Sulfate, and Magnesium Sulfate Oral Solution

For Adults

(17.5g/3.13g/1.6g) per 6 ounces

Dispense the enclosed Medication Guide to each patient.

Rx only

This carton contains:

2 6-ounce (177 mL) bottles of liquid bowel prep
1 16-ounce mixing container
1 Patient booklet. Booklet includes:1 - Medication Guide
2 - Patient Instructions
3 - Full Prescribing Information

Dilute the solution concentrate as directed prior to use.

Both 6-ounce bottles are required for a complete prep.
Store at 20°C to 25°C (68°F to 77°F). Excursions permitted between 15°C to 30°C (59°F to 86°F) [See USP controlled room temperature].

For India Manufacturing Site: